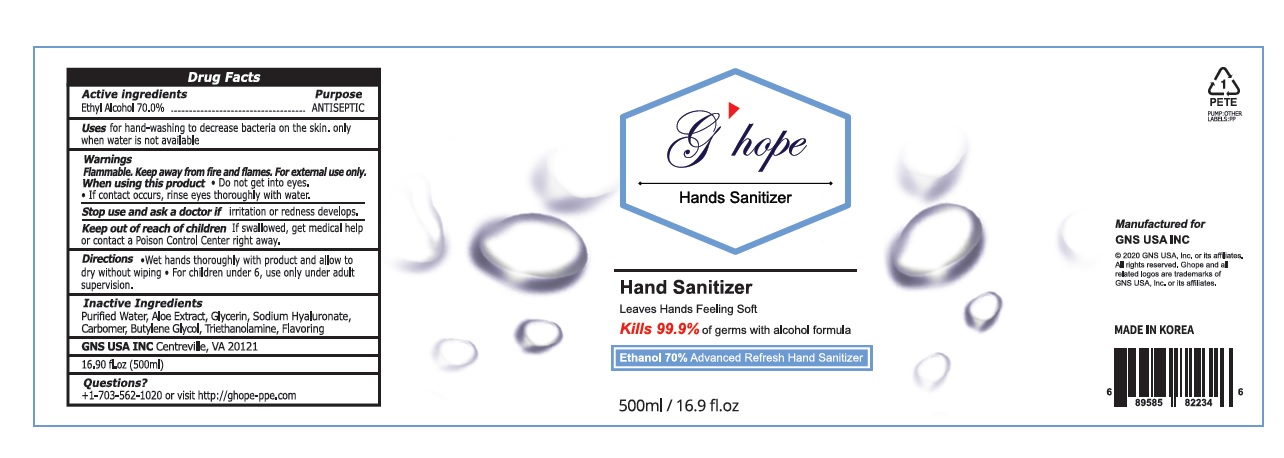 DRUG LABEL: Ghope Hands Sanitizer
NDC: 77521-500 | Form: LIQUID
Manufacturer: Gns Usa Inc.
Category: otc | Type: HUMAN OTC DRUG LABEL
Date: 20200713

ACTIVE INGREDIENTS: ALCOHOL 70 mL/100 mL
INACTIVE INGREDIENTS: WATER; ALOE; GLYCERIN; HYALURONATE SODIUM; CARBOMER HOMOPOLYMER, UNSPECIFIED TYPE; BUTYLENE GLYCOL; TROLAMINE

Ghope Hands Sanitizer

Active ingredients

Ethyl Alcohol 70.0%

Purpose

ANTISEPTIC

Uses

for hand-washing to decrease bacteria on the skin. only when water is not available

Warnings

Flammable. Keep away from fire and flames. For external use only.

When using this product • Do not get into eyes.

• If contact occurs, rinse eyes thoroughly with water.

Stop use and ask a doctor if irritation or redness develops.

Keep out of reach of children If swallowed, get medical help or contact a Poison Control Center right away.

Directions

•Wet hands thoroughly with product and allow to dry without wiping • For children under 6, use only under adult supervision.

Inactive Ingredients

Purified Water, Aloe Extract, Glycerin, Sodium Hyaluronate, Carbomer, Butylene Glycol, Triethanolamine, Flavoring

Questions?

+1-703-562-1020 or visit http://ghope-ppe.com

Leaves Hands Feeling Soft

Kills 99.9% of germs with alcohol formula

Ethanol 70% Advanced Refresh Hand Sanitizer

GNS USA INC Centreville, VA 20121

Manufactured for

GNS USA INC

© 2020 GNS USA, inc. or its affiliates.

All rights reserved. Ghope and all related logos are trademarks of GNS USA, inc. or its affiliates.

MADE IN KOREA